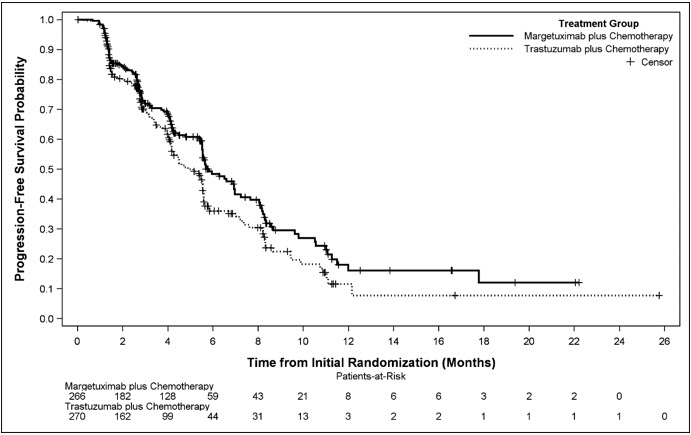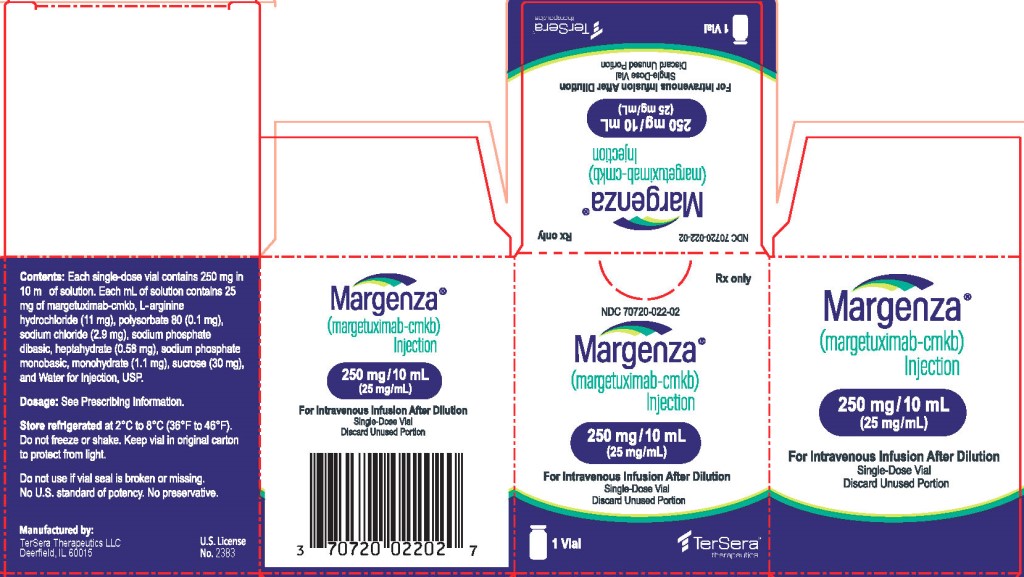 DRUG LABEL: MARGENZA
NDC: 70720-022 | Form: INJECTION, SOLUTION, CONCENTRATE
Manufacturer: TerSera Therapeutics LLC
Category: prescription | Type: HUMAN PRESCRIPTION DRUG LABEL
Date: 20250211

ACTIVE INGREDIENTS: MARGETUXIMAB 25 mg/1 mL
INACTIVE INGREDIENTS: SODIUM PHOSPHATE, MONOBASIC, MONOHYDRATE; SODIUM PHOSPHATE, DIBASIC, HEPTAHYDRATE; ARGININE HYDROCHLORIDE; SODIUM CHLORIDE; SUCROSE; POLYSORBATE 80; WATER

HIGHLIGHTS OF PRESCRIBING INFORMATION

These highlights do not include all the information needed to use MARGENZA safely and effectively. See full prescribing information for MARGENZA.
MARGENZA® (margetuximab-cmkb) injection, for intravenous use
Initial U.S. Approval: 2020

WARNING: LEFT VENTRICULAR DYSFUNCTION AND EMBRYO-FETAL TOXICITY

See full prescribing information for complete boxed warning.

Left Ventricular Dysfunction: MARGENZA may lead to reductions in left ventricular ejection fraction (LVEF). Evaluate cardiac function prior to and during treatment. Discontinue MARGENZA treatment for a confirmed clinically significant decrease in left ventricular function. (2.2, 5.1, 6.1)

Embryo-Fetal Toxicity: Exposure to MARGENZA during pregnancy can cause embryo-fetal harm. Advise patients of the risk and need for effective contraception. (5.2, 8.1, 8.3)

1 INDICATIONS AND USAGE

MARGENZA is a HER2/neu receptor antagonist indicated, in combination with chemotherapy, for the treatment of adult patients with metastatic HER2-positive breast cancer who have received two or more prior anti-HER2 regimens, at least one of which was for metastatic disease. (1, 2.1, 14.1)

2 DOSAGE AND ADMINISTRATION

For intravenous infusion only. (2.1)

Administer MARGENZA as an intravenous infusion at 15 mg/kg over 120 minutes for the initial dose, then over a minimum of 30 minutes every 3 weeks for all subsequent doses. (2.1)

On days when both MARGENZA and chemotherapy are to be administered, MARGENZA may be administered immediately after chemotherapy completion. (2.1)

3 DOSAGE FORMS AND STRENGTHS

Injection: 250 mg/10 mL (25 mg/mL) in a single-dose vial. (3)

4 CONTRAINDICATIONS

- None. (4)

5 WARNINGS AND PRECAUTIONS

- Infusion-Related Reactions (IRRs): Monitor for signs and symptoms. If a significant infusion-associated reaction occurs, slow or interrupt the infusion and administer appropriate medical therapies. (5.3)

6 ADVERSE REACTIONS

The most common adverse drug reactions (>10%) with MARGENZA in combination with chemotherapy are fatigue/asthenia, nausea, diarrhea, vomiting, constipation, headache, pyrexia, alopecia, abdominal pain, peripheral neuropathy, arthralgia/myalgia, cough, decreased appetite, dyspnea, infusion-related reactions, palmar-plantar erythrodysesthesia, and extremity pain. (6.1)

To report SUSPECTED ADVERSE REACTIONS, contact TerSera Therapeutics LLC at 1-844-334-4035 or medicalinformation@tersera.com or FDA at 1-800-FDA-1088 or www.fda.gov/medwatch.

8 USE IN SPECIFIC POPULATIONS

- Females and Males of Reproductive Potential: Verify the pregnancy status of females prior to initiation of MARGENZA. (8.3)

FULL PRESCRIBING INFORMATION

WARNING: LEFT VENTRICULAR DYSFUNCTION AND EMBRYO-FETAL TOXICITY

Left Ventricular Dysfunction: MARGENZA may lead to reductions in left ventricular ejection fraction (LVEF). Evaluate cardiac function prior to and during treatment. Discontinue MARGENZA treatment for a confirmed clinically significant decrease in left ventricular function [see Dosage and Administration (2.2), Warnings and Precautions (5.1), and Adverse Reactions (6.1)].

Embryo-Fetal Toxicity: Exposure to MARGENZA during pregnancy can cause embryo-fetal harm. Advise patients of the risk and need for effective contraception [see Warnings and Precautions (5.2), Use in Specific Populations (8.1, 8.3)].

1 INDICATIONS AND USAGE

MARGENZA is indicated, in combination with chemotherapy, for the treatment of adult patients with metastatic HER2-positive breast cancer who have received two or more prior anti-HER2 regimens, at least one of which was for metastatic disease [see Dosage and Administration (2.1) and Clinical Studies (14.1)].

2 DOSAGE AND ADMINISTRATION

2.1 Recommended Doses and Schedules

The recommended dose of MARGENZA is 15 mg/kg, administered as an intravenous infusion every 3 weeks (21-day cycle) until disease progression or unacceptable toxicity.

Administer MARGENZA as an intravenous infusion at 15 mg/kg over 120 minutes for the initial dose, then over a minimum of 30 minutes every 3 weeks for all subsequent doses.

On days when both MARGENZA and chemotherapy are to be administered, MARGENZA may be administered immediately after chemotherapy completion.

Refer to the respective Prescribing Information for each therapeutic agent administered in combination with MARGENZA for the recommended dosage information, as appropriate.

2.2 Dose Modification or Important Dosing Considerations

If a patient misses a dose of MARGENZA, administer the scheduled dose as soon as possible. Adjust the administration schedule to maintain a 3-week interval between doses.

Left Ventricular Dysfunction [see Warnings and Precautions (5.1)]

Assess left ventricular ejection fraction (LVEF) before starting MARGENZA and regularly during treatment. Withhold MARGENZA dosing for at least 4 weeks for any of the following:

- ≥ 16% absolute decrease in LVEF from pretreatment values
- LVEF below institutional limits of normal (or 50% if no limits are available) and ≥ 10% absolute decrease in LVEF from pretreatment values.

MARGENZA dosing may be resumed if, within 8 weeks, LVEF returns to normal limits and absolute decrease from baseline is ≤ 15%. Permanently discontinue MARGENZA if LVEF decline persists for greater than 8 weeks, or if dosing is interrupted on greater than 3 occasions for LVEF decline.

Infusion-Related Reactions [see Warnings and Precautions (5.3)]

Decrease the rate of infusion for mild or moderate infusion-related reactions (IRRs). Interrupt the infusion for dyspnea or clinically significant hypotension. Permanently discontinue MARGENZA dosing in patients with severe or life-threatening IRRs.

2.3 Preparation for Administration

Administer as an intravenous infusion after dilution.

Preparation for Intravenous Infusion

Prepare solution for infusion, using aseptic technique, as follows:

- Parenteral drug products should be inspected visually for particulate matter and discoloration prior to administration, whenever solution and container permit. The solution is clear to slightly opalescent, colorless to pale yellow or pale brown. Some visible, translucent, inherent proteinaceous particles may be present.
- Swirl the vial(s) gently. Do not shake the vial(s).
- Calculate the required volume of MARGENZA needed to obtain the appropriate dose according to patient's body weight. The calculated total dose volume should be rounded to the nearest 0.1 mL.
- Withdraw appropriate volume of MARGENZA solution from the vial(s) using a syringe.
- Transfer MARGENZA into an intravenous bag containing 100 mL or 250 mL 0.9% Sodium Chloride Injection, USP. Polyvinyl chloride (PVC) intravenous bags or intravenous bags made with polyolefins (polyethylene and polypropylene) and polyamide or polyolefins only or copolymer of olefins may be used. Do not use 5% Dextrose Injection, USP solution.
- The final concentration of the diluted solution should be between 0.5 mg/mL to 7.2 mg/mL.
- Gently invert the intravenous bag to mix the diluted solution. Do not shake the intravenous bag.
- Discard any unused portion left in the vial(s).

Do not administer as an intravenous push or bolus. Do not mix MARGENZA with other drugs.

Storage of Diluted Solution

- The product does not contain a preservative. If diluted infusion solution is not used immediately, it can be stored at room temperature up to 4 hours or stored refrigerated at 2°C to 8°C (36°F to 46°F) up to 24 hours. If refrigerated, allow the diluted solution to come to room temperature prior to administration. Do not freeze.

Administration

- Administer diluted infusion solution intravenously over 120 minutes for the initial dose, then over a minimum of 30 minutes every 3 weeks for all subsequent doses. Administer through an intravenous line containing a sterile, non-pyrogenic, low-protein binding polyethersulfone (PES) 0.2 micron in-line or add-on filter.
- Do not co-administer other drugs through the same infusion line.

3 DOSAGE FORMS AND STRENGTHS

Injection: 250 mg/10 mL (25 mg/mL) clear to slightly opalescent, colorless to pale yellow or pale brown solution in a single-dose vial.

4 CONTRAINDICATIONS

None.

5 WARNINGS AND PRECAUTIONS

5.1 Left Ventricular Dysfunction

Left ventricular cardiac dysfunction can occur with MARGENZA. In SOPHIA, left ventricular dysfunction occurred in 1.9% of patients treated with MARGENZA. MARGENZA has not been studied in patients with a pretreatment LVEF value of < 50%, a prior history of myocardial infarction or unstable angina within 6 months, or congestive heart failure NYHA class II-IV.

Withhold MARGENZA for ≥ 16% absolute decrease in LVEF from pretreatment values or LVEF value below institutional limits of normal (or 50% if no limits are available) and ≥ 10% absolute decrease in LVEF from pretreatment values. Permanently discontinue MARGENZA if LVEF decline persists for greater than 8 weeks, or if dosing is interrupted on greater than 3 occasions due to LVEF decline [see Dosage and Administration (2.2)].

Cardiac Monitoring

Conduct thorough cardiac assessment, including history, physical examination, and determination of LVEF by echocardiogram or MUGA scan. The following schedule is recommended:

- Baseline LVEF measurement within 4 weeks prior to initiation of MARGENZA
- LVEF measurements (MUGA/echocardiogram) every 3 months during and upon completion of MARGENZA
- Repeat LVEF measurement at 4-week intervals if MARGENZA is withheld for significant left ventricular cardiac dysfunction [see Dosage and Administration (2.2)].

5.2 Embryo-Fetal Toxicity

Based on findings in animals and mechanism of action, MARGENZA can cause fetal harm when administered to a pregnant woman. There are no available data on the use of MARGENZA in pregnant women to inform the drug-associated risk. In postmarketing reports, use of a HER2-directed antibody during pregnancy resulted in cases of oligohydramnios and oligohydramnios sequence manifesting as pulmonary hypoplasia, skeletal abnormalities and neonatal death. In an animal reproduction study, intravenous administration of margetuximab-cmkb to pregnant cynomolgus monkeys once every 3 weeks starting at gestational day (GD) 20 until delivery resulted in oligohydramnios and delayed infant kidney development. Animal exposures were ≥ 3 times the human exposures at the recommended dose, based on Cmax.

Verify pregnancy status of females of reproductive potential prior to initiation of MARGENZA. Advise pregnant women and females of reproductive potential that exposure to MARGENZA during pregnancy or within 4 months prior to conception can result in fetal harm. Advise females of reproductive potential to use effective contraception during treatment and for 4 months following the last dose of MARGENZA [see Use in Specific Populations (8.1, 8.3)].

5.3 Infusion-Related Reactions

MARGENZA can cause infusion-related reactions (IRRs) [see Adverse Reactions (6.1)]. Symptoms may include fever, chills, arthralgia, cough, dizziness, fatigue, nausea, vomiting, headache, diaphoresis, tachycardia, hypotension, pruritus, rash, urticaria, and dyspnea.

In SOPHIA, IRRs were reported by 13% of patients on MARGENZA plus chemotherapy. Most of the IRRs occur during Cycle 1. Grade 3 IRRs were reported in 1.5% of MARGENZA-treated patients. All IRRs resolved within 24 hours, irrespective of severity. In SOPHIA, IRRs leading to interruption of treatment occurred in 9% of patients treated with MARGENZA and chemotherapy. One patient (0.4%) on MARGENZA discontinued treatment due to IRR.

An infusion substudy in 88 patients in SOPHIA evaluated MARGENZA administered over 120 minutes for the initial dose, then 30 minutes from Cycle 2 forward. IRRs were ≤ Grade 2 and most occurred during the first (120 minutes) administration of MARGENZA. From Cycle 2 onward, one patient (1.1%) had an IRR (Grade 1).

Monitor patients for IRRs during MARGENZA administration and as clinically indicated after completion of infusion. Have medications and emergency equipment to treat IRRs available for immediate use. Monitor patients carefully until resolution of signs and symptoms.

In patients who experience mild or moderate IRRs, consider premedications, including antihistamines, corticosteroids, and antipyretics. Decrease the rate of infusion for mild or moderate IRRs. Interrupt MARGENZA infusion in patients experiencing dyspnea or clinically significant hypotension and intervene with medical therapy which may include epinephrine, corticosteroids, diphenhydramine, bronchodilators and oxygen. Patients should be evaluated and carefully monitored until complete resolution of signs and symptoms. Permanently discontinue MARGENZA in all patients with severe or life-threatening IRRs.

6 ADVERSE REACTIONS

The following adverse reactions are discussed in greater detail in other sections of the label:

- Left Ventricular Dysfunction [see Warnings and Precautions (5.1)]
- Embryo-Fetal Toxicity [see Warnings and Precautions (5.2)]
- Infusion-Related Reactions [see Warnings and Precautions (5.3)]

6.1 Clinical Trials Experience

Because clinical trials are conducted under widely varying conditions, adverse reaction rates observed in the clinical trials of a drug cannot be directly compared to rates in the clinical trials of another drug and may not reflect rates observed in practice.

The safety of MARGENZA was evaluated in HER2-positive breast cancer patients who received two or more prior anti-HER2 regimens in SOPHIA [see Clinical Studies (14.1)].

Patients were randomized (1:1) to receive either MARGENZA 15 mg/kg every 3 weeks plus chemotherapy or trastuzumab plus chemotherapy. Among patients who received MARGENZA, 40% were exposed for 6 months or longer and 11% were exposed for greater than one year.

Serious adverse reactions occurred in 16% of patients who received MARGENZA. Serious adverse reactions in > 1% of patients included febrile neutropenia (1.5%), neutropenia/neutrophil count decrease (1.5%) and infusion related reactions (1.1%). Fatal adverse reactions occurred in 1.1% of patients who received MARGENZA, including viral pneumonia (0.8%) and aspiration pneumonia (0.4%).

Permanent discontinuation due to an adverse reaction occurred in 3% of patients who received MARGENZA. Adverse reactions which resulted in permanent discontinuation in > 1% of patients who received MARGENZA included left ventricular dysfunction and infusion-related reactions.

Dosage interruptions due to an adverse reaction occurred in 11% of patients who received MARGENZA. Adverse reactions which required dosage interruption in > 5% of patients who received MARGENZA included infusion-related reactions.

Table 1 summarizes the adverse reactions in SOPHIA.

Table 1 Adverse Reactions (>10%) in Patients with Metastatic HER2-Positive Breast Cancer Who Received MARGENZA in SOPHIA
Adverse Reaction | MARGENZA + Chemotherapy (n = 264) |  | Trastuzumab + Chemotherapy (n = 266)
 | All Grades (%) | Grade 3 or 4 (%) | All Grades (%) | Grade 3 or 4 (%)
General disorders and administration site conditions
Fatigue/Asthenia | 57 | 7 | 47 | 4.5
Pyrexia | 19 | 0.4 | 14 | 0.4
Gastrointestinal disorders
Nausea | 33 | 1.1 | 32 | 0.4
Diarrhea | 25 | 2.3 | 25 | 2.3
Vomiting | 21 | 0.8 | 14 | 1.5
Constipation | 19 | 0.8 | 17 | 0.8
Abdominal pain [Includes abdominal pain, abdominal discomfort, lower abdominal pain and upper abdominal pain] | 17 | 1.5 | 21 | 1.5
Skin and Subcutaneous tissue
Alopecia | 18 | 0 | 15 | 0
Palmar-plantar erythrodysesthesia | 13 | 0 | 15 | 3
Nervous System Disorders
Headache [Includes headache and migraine] | 19 | 0 | 16 | 0
Peripheral neuropathy [Includes peripheral neuropathy, peripheral sensory neuropathy, peripheral motor neuropathy, and neuropathy] | 16 | 1.1 | 15 | 2.3
Respiratory, thoracic and mediastinal disorders
Cough | 14 | 0.4 | 12 | 0
Dyspnea | 13 | 1.1 | 11 | 2.3
Metabolism and nutrition disorders
Decreased appetite | 14 | 0.4 | 14 | 0.4
Musculoskeletal and connective tissue disorders
Arthralgia/Myalgia | 14 | 0.4 | 12 | 0.8
Extremity pain | 11 | 0.8 | 9 | 0
Injury, poisoning and procedural complications
Infusion-related reaction | 13 | 1.5 | 3 | 0

Clinically relevant adverse reactions in ≤10% of patients who received MARGENZA in combination with chemotherapy included: dizziness and stomatitis (10%) each, decreased weight, dysgeusia, rash, and insomnia (6%) each, hypertension (5%), and syncope (1.5%).

Table 2 summarizes the laboratory abnormalities in SOPHIA.

Table 2 Select Laboratory Abnormalities (≥20%) That Worsened from Baseline in Patients with Metastatic HER2-Positive Breast Cancer Who Received MARGENZA in SOPHIA
Laboratory Abnormality | MARGENZA + Chemotherapy [The denominator used to calculate the rate varied from 229 to 253 based on the number of patients with a baseline value and at least one post-treatment value.] |  | Trastuzumab + Chemotherapy
 | All Grades (%) | Grade 3 or 4 (%) | All Grades (%) | Grade 3 or 4 (%)
Hematology
Decreased hemoglobin | 52 | 3.2 | 43 | 2.4
Decreased leukocytes | 40 | 5 | 36 | 3.2
Decreased neutrophils | 34 | 9 | 28 | 9
Increased aPTT | 32 | 3.4 | 34 | 4.3
Decreased lymphocytes | 31 | 4.4 | 38 | 4.4
Increased INR | 24 | 1.2 | 25 | 0.4
Chemistry
Increased creatinine | 68 | 0.4 | 60 | 0
Increased ALT | 32 | 2 | 30 | 0.8
Increased lipase | 30 | 6 | 24 | 3.2
Increased AST | 23 | 2 | 22 | 0.8
Increased alkaline phosphatase | 21 | 0 | 23 | 0.8
aPTT: activated partial thromboplastin time; INR: prothrombin international normalized ratio; ALT: alanine aminotransferase; AST: aspartate aminotransferase

7 DRUG INTERACTIONS

Anthracyclines

Patients who receive anthracyclines less than 4 months after stopping MARGENZA [see Clinical Pharmacology (12.3)] may be at increased risk of cardiac dysfunction. While this interaction has not been studied with MARGENZA, clinical data from other HER2-directed antibodies warrants consideration. Avoid anthracycline-based therapy for up to 4 months after stopping MARGENZA. If concomitant use is unavoidable, closely monitor patient's cardiac function.

8 USE IN SPECIFIC POPULATIONS

8.1 Pregnancy

Risk Summary

Based on findings in animals and mechanism of action, MARGENZA can cause fetal harm when administered to a pregnant woman. There are no available data on use of MARGENZA in pregnant women to inform the drug-associated risk. In postmarketing reports, use of a HER2-directed antibody during pregnancy resulted in cases of oligohydramnios and oligohydramnios sequence manifesting as pulmonary hypoplasia, skeletal abnormalities, and neonatal death. In an animal reproduction study, intravenous administration of margetuximab-cmkb to pregnant cynomolgus monkeys once every 3 weeks, starting at gestational day (GD) 20 until delivery, resulted in oligohydramnios and delayed infant kidney development. Animal exposures were ≥ 3 times the human exposures at the recommended dose, based on Cmax (see Data). Advise patients of potential risks to a fetus. There are clinical considerations if MARGENZA is used during pregnancy or within 4 months prior to conception (see Clinical Considerations).

Estimated background risk of major birth defects and miscarriage for the indicated population is unknown. In the U.S. general population, background risks of major birth defects and miscarriage in clinically recognized pregnancies are 2 - 4% and 15 - 20%, respectively.

Clinical Considerations

Fetal/Neonatal Adverse Reactions

Monitor women who received MARGENZA during pregnancy or within 4 months prior to conception for oligohydramnios. If oligohydramnios occurs, perform fetal testing that is appropriate for gestational age and consistent with community standards of care.

Data

Animal Data

In an enhanced pre- and post-natal development study, pregnant cynomolgus monkeys received intravenous doses of 50 or 100 mg/kg margetuximab-cmkb once every 3 weeks starting on GD 20 and until delivery. Animal exposures at doses of 50 and 100 mg/kg were 3 and 6 times, respectively, the human exposures at the recommended dose, based on Cmax. Treatment with 50 and 100 mg/kg margetuximab-cmkb resulted in oligohydramnios beginning on GD 75.

An infant mortality occurred on post-natal day 63 following maternal exposure to 100 mg/kg margetuximab-cmkb. Clinical findings included tubular degeneration/necrosis and tubular dilatation in the kidney. Maternal doses of 50 and 100 mg/kg resulted in decreased infant kidney weights and histologic immature nephrons. Measurable serum concentrations of margetuximab-cmkb were observed in infant animals, which is consistent with margetuximab-cmkb crossing the placenta.

8.2 Lactation

Risk Summary

There is no information regarding presence of MARGENZA in human milk, effects on the breastfed child, or effects on milk production. Published data suggest human IgG is present in human milk but does not enter neonatal or infant circulation in substantial amounts. Consider developmental and health benefits of breastfeeding along with the mother's clinical need for MARGENZA treatment and any potential adverse effects on the breastfed child from MARGENZA or from the underlying maternal condition. This consideration should also take into account the MARGENZA washout period of 4 months [see Clinical Pharmacology (12.3)].

8.3 Females and Males of Reproductive Potential

MARGENZA can cause fetal harm when administered to a pregnant woman.

Pregnancy Testing

Verify pregnancy status of females of reproductive potential prior to initiation of MARGENZA.

Contraception

Females

Advise females of reproductive potential to use effective contraception during treatment and for 4 months following the last dose of MARGENZA [see Use in Specific Populations (8.1) and Clinical Pharmacology (12.3)].

8.4 Pediatric Use

Safety and effectiveness of MARGENZA have not been established in pediatric patients.

8.5 Geriatric Use

Of the 266 patients treated with MARGENZA 20% were 65 years of age or older and 4% were 75 years or older. No overall differences in efficacy were observed between patients ≥ 65 years of age compared to younger patients. There was a higher incidence of Grade ≥ 3 adverse reactions observed in patients age 65 years or older (56%) compared to younger patients (47%), as well as adverse reactions associated with potential cardiotoxicity (35% vs 18%).

11 DESCRIPTION

Margetuximab-cmkb, a HER2/neu receptor antagonist, is a chimeric Fc-engineered IgG1 kappa monoclonal antibody.

Margetuximab-cmkb is produced by recombinant DNA technology in a mammalian cell (Chinese Hamster Ovary) culture. Margetuximab-cmkb has an approximate molecular weight of 149 kDa.

MARGENZA (margetuximab-cmkb) injection is a sterile, preservative-free, clear to slightly opalescent, colorless to pale yellow or pale brown solution that requires dilution for intravenous use. Some visible, translucent, inherent proteinaceous particles may be present. Each single-dose vial contains 250 mg of margetuximab-cmkb in 10 mL of solution. Each mL of solution contains 25 mg of margetuximab-cmkb, L-arginine hydrochloride (11 mg), polysorbate 80 (0.1 mg), sodium chloride (2.9 mg), sodium phosphate dibasic, heptahydrate (0.58 mg), sodium phosphate monobasic, monohydrate (1.1 mg), sucrose (30 mg), and Water for Injection, USP at a pH of approximately 6.1.

12 CLINICAL PHARMACOLOGY

12.1 Mechanism of Action

Margetuximab-cmkb binds to the extracellular domain of the human epidermal growth factor receptor 2 protein (HER2). Upon binding to HER2-expressing tumor cells, margetuximab-cmkb inhibits tumor cell proliferation, reduces shedding of the HER2 extracellular domain and mediates antibody-dependent cellular cytotoxicity (ADCC).

In vitro, the modified Fc region of margetuximab-cmkb increases binding to activating Fc receptor FCGR3A (CD16A) and decreases binding to inhibitory Fc receptor FCGR2B (CD32B). These changes lead to greater in vitro ADCC and NK cell activation.

12.2 Pharmacodynamics

The exposure-response relationship and time course of pharmacodynamic response for the safety and effectiveness of margetuximab-cmkb have not been fully characterized.

12.3 Pharmacokinetics

Following the approved recommended dosage, the steady-state geometric mean (%CV) Cmax of margetuximab-cmkb is 466 (20%) µg/mL and AUC0-21d is 4120 (21%) µg.day/mL in patients with HER2-positive relapsed or refractory advanced breast cancer. Margetuximab-cmkb undergoes both linear and nonlinear elimination. After a single dose, margetuximab-cmkb Cmax and AUC0-21d increase in an approximately dose proportional manner from 10 to 18 mg/kg (0.67 to 1.2 times the approved recommended dose). At the approved recommended dosage, time to steady-state was 2 months, and accumulation ratio was 1.65 based on AUC0-21d. No clinically significant differences in margetuximab-cmkb exposure were observed when infusion time was reduced from 120 minutes to 30 minutes.

Distribution

Margetuximab-cmkb geometric mean (%CV) steady-state volume of distribution is 5.47 L (22%).

Elimination

The geometric mean (%CV) terminal half-life of margetuximab-cmkb is 19.2 days (28%) and clearance is 0.22 L/day (24%). Four months after margetuximab-cmkb discontinuation, concentrations decrease to approximately 3% of the steady-state trough serum concentration.

Metabolism

Margetuximab-cmkb is expected to be metabolized into small peptides by catabolic pathways.

Specific Populations

No clinically significant differences in margetuximab-cmkb PK were observed based on age (29 to 83 years), sex, race (Caucasian, Black, Asian), mild to moderate (CLcr 30 to 89 mL/min estimated using the Cockcroft-Gault equation) renal impairment, mild hepatic impairment (total bilirubin ≤ ULN and AST > ULN, or total bilirubin 1 to 1.5 ULN and any AST), HER2 expression level (0 to 3 by IHC), tumor burden (2 – 317 mm), ECOG score (0 to 2), albumin (24 to 50 g/L), FCGR3A (CD16A), FCGR2A (CD32A) and FCGR2B (CD32B) genotype, number of metastatic sites (≤ 2 or > 2), number of prior therapy lines (≤ 2 or > 2) or concurrent chemotherapies (capecitabine, gemcitabine, eribulin and vinorelbine).

The effect of severe renal impairment (CLcr 15 to 29 mL/min), end-stage renal disease with or without hemodialysis, and moderate (total bilirubin > 1.5 to ≤ 3 ULN and any AST) or severe hepatic impairment (total bilirubin >3 ULN and any AST) on margetuximab-cmkb PK is unknown.

12.6 Immunogenicity

The observed incidence of anti-drug antibodies is highly dependent on the sensitivity and specificity of the assay. Differences in assay methods preclude meaningful comparisons of the incidence of anti-drug antibodies in the studies described below with the incidence of anti-drug antibodies in other studies, including those of MARGENZA or of other margetuximab products.

In patients who received MARGENZA in combination with chemotherapy in SOPHIA (up to 68 months) or the Infusion substudy (up to 42 months), the incidence of anti-margetuximab antibodies was 2% (7/350). No patients developed treatment-emergent neutralizing antibodies.

Given the low incidence of anti-margetuximab antibodies, the effect of anti-margetuximab antibodies on the pharmacokinetics, pharmacodynamics, safety, and/or effectiveness of margetuximab-cmkb is unknown.

13 NONCLINICAL TOXICOLOGY

13.1 Carcinogenesis, Mutagenesis, and Impairment of Fertility

Studies have not been performed to evaluate carcinogenic or mutagenic potential of margetuximab-cmkb.

Animal fertility studies have not been conducted with margetuximab-cmkb. In repeat-dose toxicity studies of up to 13-week duration, margetuximab-cmkb had no effect on male and female reproductive organs in sexually mature cynomolgus monkeys.

14 CLINICAL STUDIES

14.1 Metastatic Breast Cancer

The efficacy of MARGENZA plus chemotherapy was evaluated in SOPHIA (NCT02492711), a randomized, multicenter, open-label trial of 536 patients with IHC 3+ or ISH-amplified HER2+ metastatic breast cancer who had received prior treatment with other anti-HER2 therapies. Patients were randomized (1:1) to MARGENZA plus chemotherapy or trastuzumab plus chemotherapy. Randomization was stratified by chemotherapy choice (capecitabine, eribulin, gemcitabine, or vinorelbine), number of lines of therapy in the metastatic setting (≤ 2, > 2), and number of metastatic sites (≤ 2, > 2). Patients were required to have progressed on or after the most recent line of therapy. Prior radiotherapy and hormonal therapy were allowed. Patients received MARGENZA intravenously at a dose of 15 mg/kg every 3 weeks administered over 120 minutes for the initial administration and then over 30 to 120 minutes thereafter. Trastuzumab was given intravenously at an initial dose of 8 mg/kg over 90 minutes, followed by 6 mg/kg over 30 minutes every 3 weeks thereafter. Patients were treated with MARGENZA or trastuzumab in combination with chemotherapy until disease progression or unacceptable toxicity.

Major efficacy outcome measures were progression-free survival (PFS) by blinded independent central (BICR) review and overall survival (OS) of MARGENZA plus chemotherapy, compared with trastuzumab plus chemotherapy. Additional efficacy outcome measures were objective response rate (ORR) and duration of response (DOR) assessed by BICR.

The median age was 56 years (range: 27-86); 78% of patients were < 65 years. The majority of patients were female (99.4%), and the majority were White (80%). Patients had an ECOG performance status of 0 (58%) or 1 (42%) at baseline. Forty seven percent had visceral disease, 57% had bone metastases, and 13% had brain metastases. Sixty percent were hormone receptor positive. The median number of prior lines of therapy in the locally advanced/metastatic setting was 2 (range: 1-4). All study patients had previously received trastuzumab, all but 1 patient had previously received pertuzumab, and 91% had previously received ado-trastuzumab emtansine.

Efficacy results are summarized in Table 3 and Figure 1.

Table 3 Efficacy Results in SOPHIA
 | MARGENZA + Chemotherapy (n = 266) | Trastuzumab + Chemotherapy (n = 270)
Progression-free Survival [Assessed per BICR.]
Number of events (%) | 130 (48.9) | 135 (50.0)
Disease progression | 118 (44.4) | 125 (46.3)
Death | 12 (4.5) | 10 (3.7)
Median, months (95% CI) [Based on Kaplan-Meier estimates.] | 5.8 (5.5, 7.0) | 4.9 (4.2, 5.6)
Hazard Ratio (HR) (95% CI) [Based on stratified Cox Model.] | 0.76 (0.59, 0.98)
p-value [p-value based on 2-sided stratified log rank test.] | 0.033
Overall Survival
Number of events (%) | 194 (72.9) | 191 (70.7)
Median, months (95% CI) | 21.6 (18.9, 25.1) | 21.9 (18.7, 24.2)
Hazard Ratio (HR) (95% CI) | 0.95 (0.77, 1.17)
p-value | 0.620 [Not statistically significant]
Objective Response for Patients with Measurable Disease | (n = 262) | (n = 262)
Confirmed Objective Response Rate (95% CI) | 22 (17, 27) | 16 (12, 20)
Duration of Objective Response | (n = 58) | (n = 42)
Median (months) (95% CI) | 6.1 (4.1, 9.1) | 6.0 (4.0, 6.9)
CI: confidence interval; n: number of patients.

Figure 1 Kaplan-Meier Curve for Progression-Free Survival in SOPHIA

Results for investigator-assessed PFS were similar to the independent blinded PFS results.

Consistent PFS results were observed across patient subgroups defined by study stratification factors (chemotherapy choice, number of lines of therapy in the metastatic setting, and number of metastatic sites).

16 HOW SUPPLIED/STORAGE AND HANDLING

16.1 How Supplied

MARGENZA (margetuximab-cmkb) injection is a clear to slightly opalescent, colorless to pale yellow or pale brown solution in a single-dose vial supplied as:

Carton Contents | NDC
One 250 mg/10 mL (25 mg/mL) single-dose vial | NDC 70720-022-02
Four 250 mg/10 mL (25 mg/mL) single-dose vials | NDC 70720-022-03

16.2 Storage

Store vials refrigerated at 2°C to 8°C (36°F to 46°F) in original carton to protect from light until time of use.

Do not freeze. Do not shake.

17 PATIENT COUNSELING INFORMATION

Left Ventricular Dysfunction

Advise patients to contact a health care professional immediately for any of the following: new onset or worsening shortness of breath, cough, swelling of the ankles/legs, swelling of the face, palpitations, weight gain of more than 5 pounds in 24 hours, dizziness or loss of consciousness [see Warnings and Precautions (5.1)].

Embryo-Fetal Toxicity

Advise pregnant women and females of reproductive potential that exposure to MARGENZA during pregnancy or within 4 months prior to conception can result in fetal harm. Advise female patients to contact their healthcare provider with a known or suspected pregnancy [see Warnings and Precautions (5.2), Use in Specific Populations (8.1)].

Advise females of reproductive potential to use effective contraception during treatment with MARGENZA and for 4 months following the last dose [see Warnings and Precautions (5.2), Use in Specific Populations (8.3)].

MARGENZA® (margetuximab-cmkb)

Manufactured by:
TerSera Therapeutics LLC
Deerfield, IL 60015
U.S. License No. 2383

MARGENZA® is a registered trademark of TerSera Therapeutics LLC
©2025 TerSera Therapeutics LLC

PRINCIPAL DISPLAY PANEL - 250 mg/10 mL Vial Carton

Rx only

NDC 70720-022-02

Margenza®
(margetuximab-cmkb)
Injection

250 mg/10 mL
(25 mg/mL)

For Intravenous Infusion After Dilution
Single-Dose Vial
Discard Unused Portion

1 Vial
TerSera therapeutics